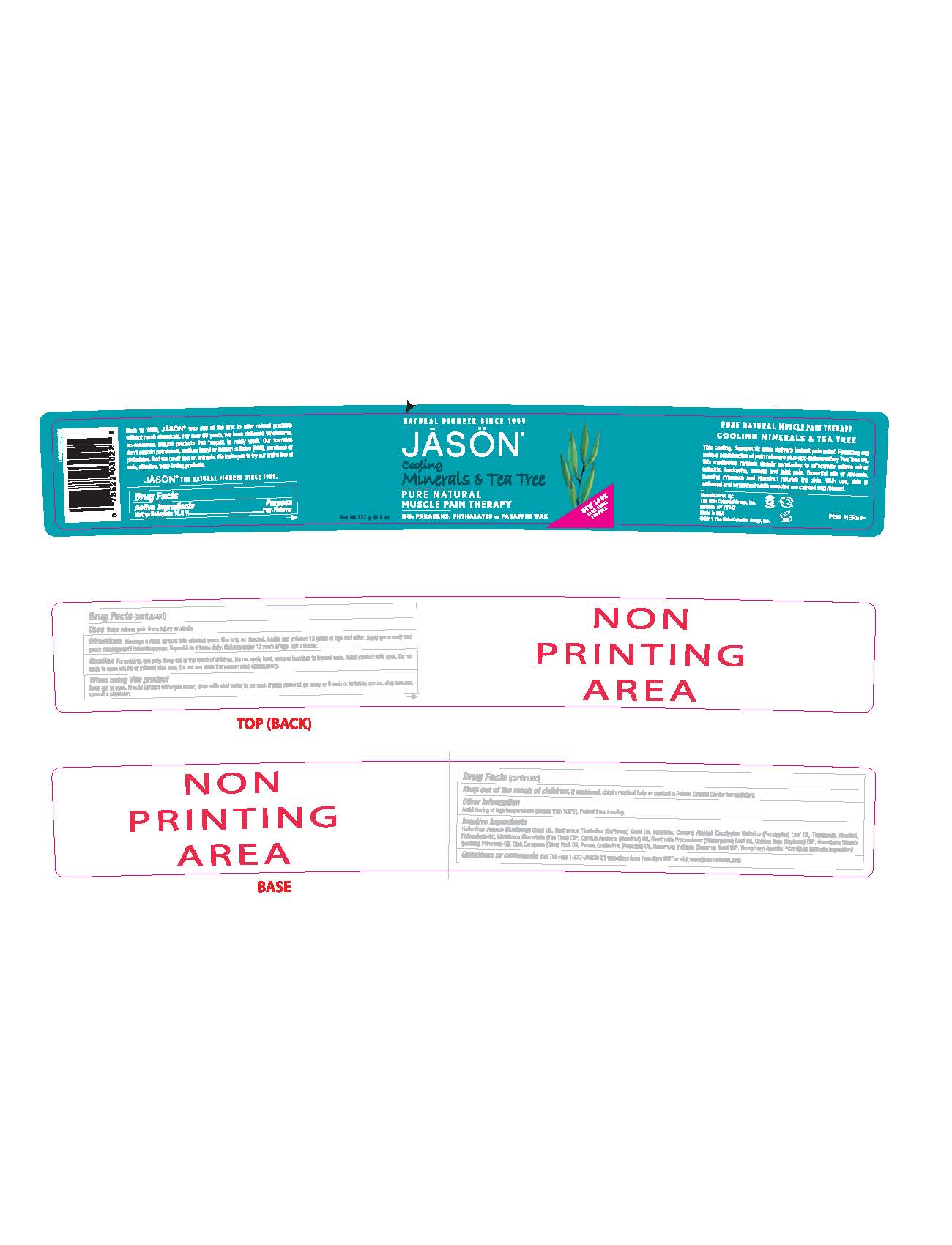 DRUG LABEL: Jason Cooling Minerals and Tea Tree Pain Therapy
NDC: 61995-0602 | Form: OINTMENT
Manufacturer: The Hain Celestial Group, Inc
Category: otc | Type: HUMAN OTC DRUG LABEL
Date: 20120529

ACTIVE INGREDIENTS: METHYL SALICYLATE 13.5 g/100 g
INACTIVE INGREDIENTS: SUNFLOWER OIL; YELLOW WAX; EUCALYPTUS OIL; CETOSTEARYL ALCOHOL; TRIBEHENIN ; MENTHOL; POLYSORBATE 60 ; TEA TREE OIL ; EUROPEAN HAZELNUT OIL; SOYBEAN OIL; EVENING PRIMROSE OIL; OLIVE OIL; AVOCADO OIL; SESAME OIL; .ALPHA.-TOCOPHEROL ACETATE; SAFFLOWER OIL 

Drug Facts

ACTIVE INGREDIENT

Methyl Salicylate 13.5%

PURPOSE

Pain Reliver

INDICATIONS AND USAGE

- Helps relieve pain from injury or strain

WARNINGS

For external use only. Keep out of reach of children. Do not apply heat, wrap or bandage to treated area. Avoid contact with eyes. Do not apply to open wound or irritated skin area. Do not use more than seven days continuously. Should contact with eyes occurs, rinse with cool water to remove. If pain does not go away or rash or irritation occurs, stop use and contact a physician.

Keep out of reach of children. If swallowed get medical help or contact Poison Center immediately.

DOSAGE AND ADMINISTRATION

Massage a small amount into affected area. Use only as directed. Adult and children 12 years of age and older: Apply generously and gentle massage until balm disappeared. Repeat 3 to 4 times daily. Children under 2 years of age ask a doctor.

INACTIVE INGREDIENT

Helianthus Annuus (Sunflower) Seed Oil (1), Carthamus Tinctorius (Safflower) Seed Oil (1), Beeswax (1), Cetearyl Alcohol, Eucalyptus Globulus (Eucalyptus) Leaf Oil, Tribehenin, Menthol, Polysorbate 60, Malaleuca Alternifolia (Tea Tree) Oil(1), Corylus Avellana (Hazelnut) Oil, Gaultheria Procumbens (Wintergreen) Leaf Oil, Glycine Soja (Soybean) Oil (1), Oenothera Biennis (Evening Primrose) Oil, Olea Europaea (Olive) Fruit Oil, Persea Gratissima (Avocado) Oil, Sesamum Indicum (Sesame) Seed Oil (1), Tocopheryl Acetate.

(1) Certified Organic Ingredients

QUESTIONS

Questions? Visit www.jason-natural.com or call 1-877-527-Jason-01weekdays from 7am-5pm MST.